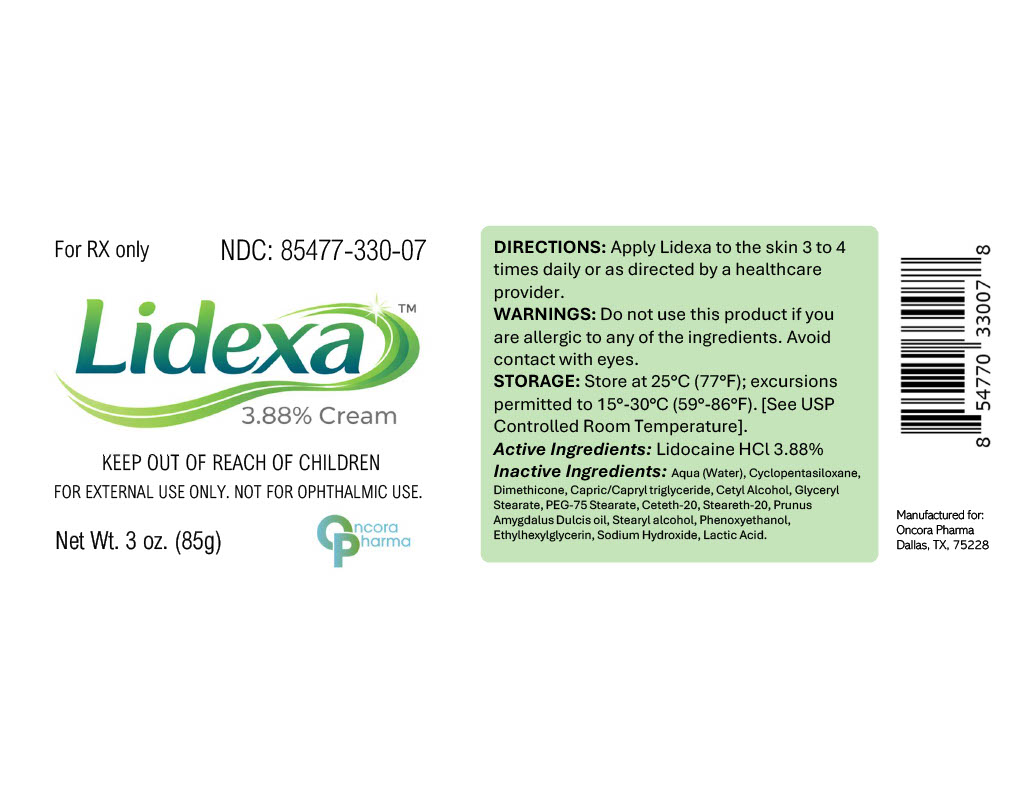 DRUG LABEL: Lidexa
NDC: 85477-330 | Form: CREAM
Manufacturer: Oncora Pharma, LLC
Category: prescription | Type: HUMAN PRESCRIPTION DRUG LABEL
Date: 20260227

ACTIVE INGREDIENTS: LIDOCAINE 38.8 mg/1 g

Lidexa

DESCRIPTION

Lidexa™ (Lidocaine Hydrochloride) Cream 38.8

INDICATIONS AND USAGE

Lidexa™ is indicated for topical analgesia as directed by a healthcare provider.

CONTRAINDICATIONS

Lidexa™ is contraindicated in patients with known hypersensitivity to lidocaine or any component of the formulation.

WARNINGS

For external use only. Not for ophthalmic use.
Avoid contact with eyes.
Excessive application may result in increased systemic absorption.
Keep out of reach of children.

PRECAUTIONS

Use only as directed. If irritation occurs, discontinue use and consult a healthcare provider.

ADVERSE REACTIONS

Localized skin reactions such as redness, irritation, or rash may occur.

DOSAGE AND ADMINISTRATION

For topical use only.
Apply to the affected area 3 to 4 times daily or as directed by a healthcare provider.

HOW SUPPLIED

Lidexa™ (Lidocaine Hydrochloride 38.8 mg/g) is supplied as a white topical cream in a 3 oz (85 g) tube.
NDC 85477-330-07

PRINCIPAL DISPLAY PANEL

pdp